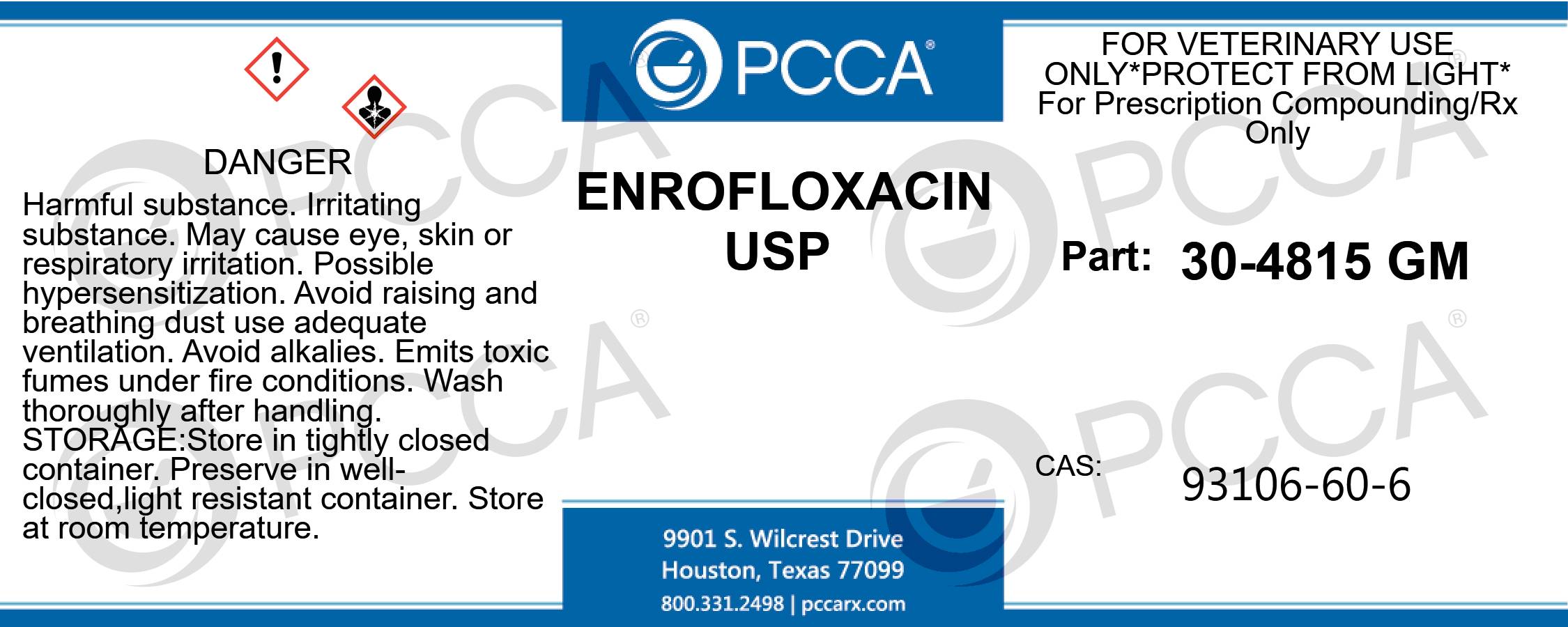 DRUG LABEL: ENROFLOXACIN
NDC: 51927-0258 | Form: POWDER
Manufacturer: Professional Compounding Centers of America dba PCCA
Category: other | Type: BULK INGREDIENT - ANIMAL DRUG
Date: 20221117

ACTIVE INGREDIENTS: ENROFLOXACIN 1 kg/1 kg

30-4815 ENROFLOXACIN USP 51927-0258-0

ENROFLOXACIN USP FOR VETERINARY USE ONLY *PROTECT FROM LIGHT* For Prescription Compounding/Rx Only PART: 30-4815 GM CAS: 93106-60-6 DANGER: HARMFUL SUBSTANCE. IRRITATING SUBSTANCE. MAY CAUSE EYE, SKIN OR RESPIRATORY IRRITATION. POSSIBLE HYPERSENSITIZATION. AVOID RAISING AND BREATHING DUST USE ADEQUATE VENTILATION. AVOID ALKALIES. EMITS TOXIC FUMES UNDER FIRE CONDITIONS. WASH THOROUGHLY AFTER HANDLING. STORE IN TIGHTLY CLOSED CONTAINER. PRESERVE IN WELL-CLOSED,LIGHT RESISTANT CONTAINER. STORE AT ROOM TEMPERATURE.

ENROFLOXACIN USP
FOR VETERINARY USE ONLY *PROTECT FROM LIGHT*
For Prescription Compounding/Rx Only
PART: 30-4815 GM
CAS: 93106-60-6
DANGER: HARMFUL SUBSTANCE. IRRITATING SUBSTANCE. MAY CAUSE EYE, SKIN OR RESPIRATORY IRRITATION. POSSIBLE HYPERSENSITIZATION. AVOID RAISING AND BREATHING DUST USE ADEQUATE VENTILATION. AVOID ALKALIES. EMITS TOXIC FUMES UNDER FIRE CONDITIONS. WASH THOROUGHLY AFTER HANDLING. STORE IN TIGHTLY CLOSED CONTAINER. PRESERVE IN WELL-CLOSED,LIGHT RESISTANT CONTAINER. STORE AT ROOM TEMPERATURE.